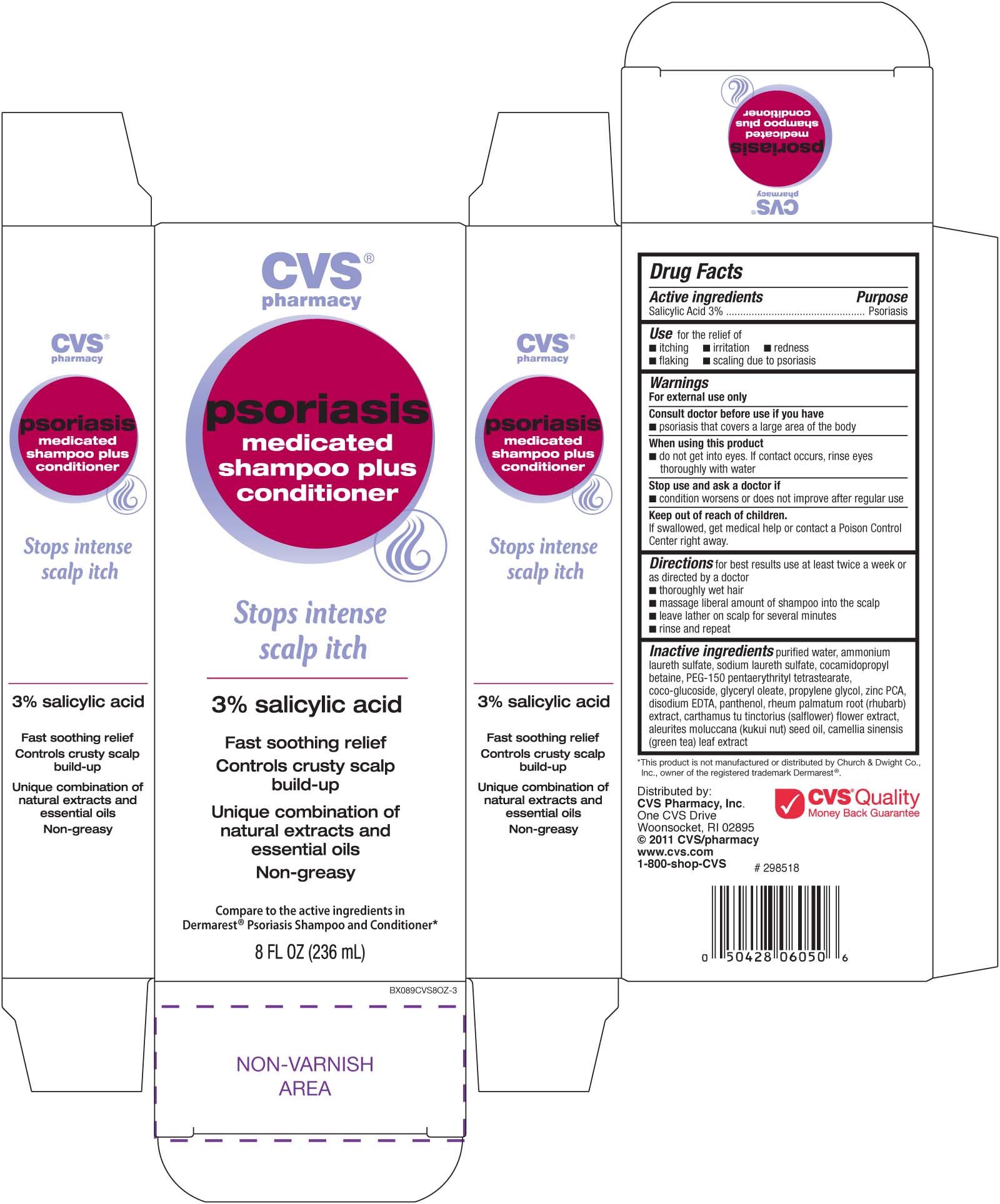 DRUG LABEL: CVS Psoriasis Medicated 
NDC: 59779-316 | Form: SHAMPOO
Manufacturer: CVS Pharmacy
Category: otc | Type: HUMAN OTC DRUG LABEL
Date: 20100716

ACTIVE INGREDIENTS: SALICYLIC ACID 30 mg/1 mL
INACTIVE INGREDIENTS: WATER; AMMONIUM LAURYL SULFATE; COCAMIDOPROPYL BETAINE; SODIUM LAURETH SULFATE; CITRIC ACID MONOHYDRATE; LAURYL GLUCOSIDE; GLYCERYL MONOOLEATE; ZINC PIDOLATE; PEG-150 DISTEARATE; KUKUI NUT OIL; PANTHENOL; EDETATE DISODIUM; RHUBARB; GREEN TEA LEAF; SUNFLOWER SEED; PROPYLENE GLYCOL

drug facts

Active ingredient Purpose
Salicylic Acid (3%)..................................Psoriasis

PURPOSE

Use for the relief of
- itching - irritation - redness - flaking - scaling due to proriasis

Keep out of reach of children. If swallowed, get medical help
or contact a Poison Control Center right away.

INDICATIONS AND USAGE

Use for the relief of
- itching - irritation - redness - flaking - scaling due to proriasis

Directions for best results use at least twice a week or as directed by a doctor

- thoroughly wet hair

- Massage liberal amount of shampoo into the scalp

- Leave lather on scalp for several minutes

- Rinse and repeat.

Warnings For external use only.
Ask a doctor before use if you have
- psoriasis that covers a large area of the body.
When using this product
- do not get into eyes. If contact occurs, rinse eyes thoroughly with water
Stop use and ask a doctor if
- condition worsens or does not improve after regular use
Keep out of reach of children.
If swallowed, get medical help or contact a Poison Control Center right away.

DOSAGE AND ADMINISTRATION

Directions - for best results, use at least twice a week or as directed by a doctor.

- Wet hair thoroughly. - Massage a liberal amount into your scalp.

- Leave lather on scalp for several minutes - Rinse and repeat.

Inactive Ingredients
purified water, ammonium Laureth sulfate, cocoamidopropyl betaine, PEG-150 pentaerythrityl tetrastearate,
coco-glucoside, glyceryl oleate, propylene glycol, zinc PCA, disodium EDTA, panthenol, rheum palmatum root
(rubarb) extract, carthamus tu tinctorius (salflower) flower extract, aleurites moluccana (kukui nut) seed oil, camellia
sinensis (green tea) leaf extract